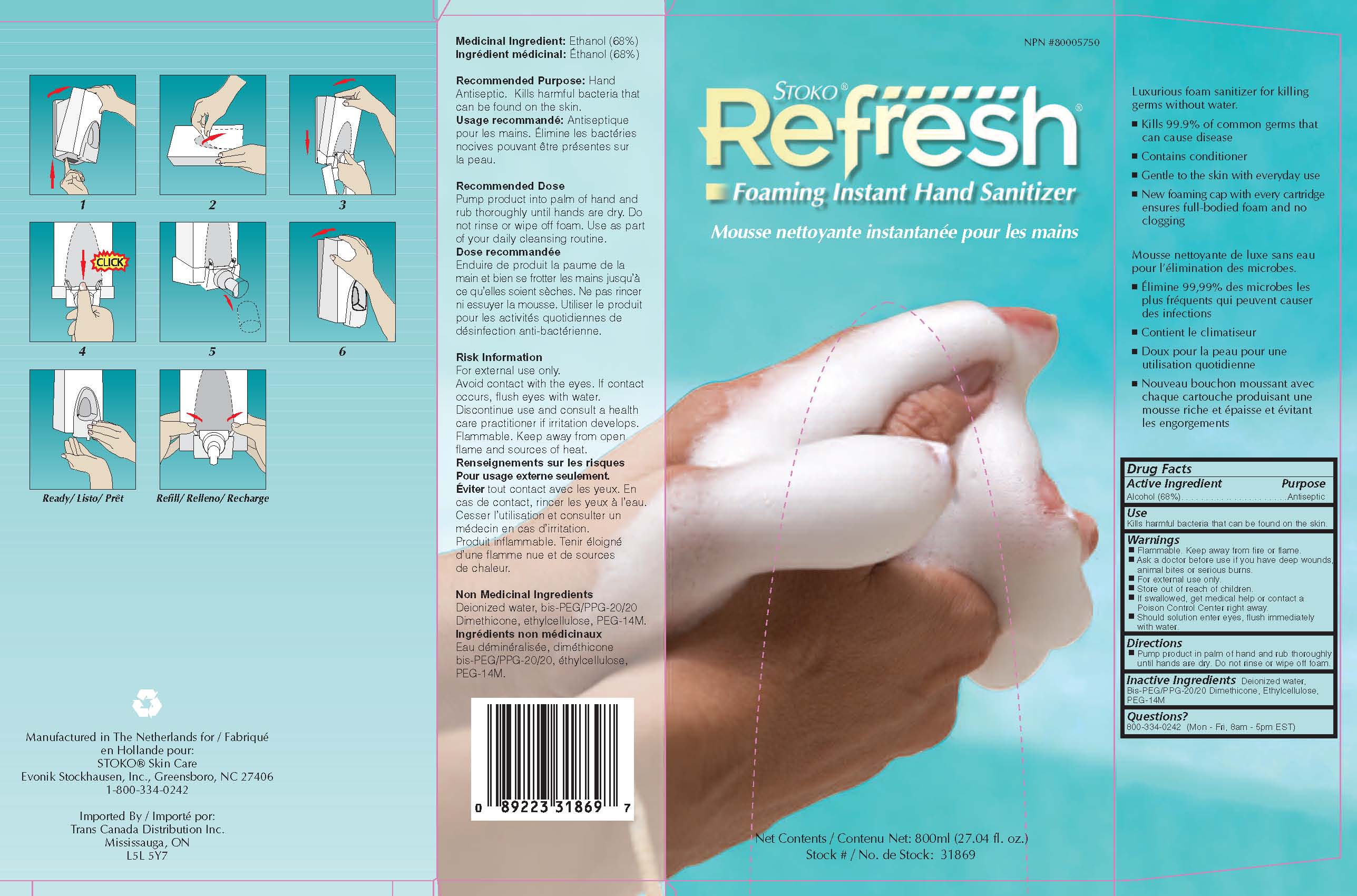 DRUG LABEL: Refresh Foaming Instant Hand Sanitizer
NDC: 64064-050 | Form: LIQUID
Manufacturer: Evonik Stockhausen, LLC
Category: otc | Type: HUMAN OTC DRUG LABEL
Date: 20111026

ACTIVE INGREDIENTS: ALCOHOL 68 mL/100 mL
INACTIVE INGREDIENTS: WATER; POLYETHYLENE GLYCOL 14000; ETHYLCELLULOSES

Drug Facts

ACTIVE INGREDIENT

Ethanol (68%)

PURPOSE

Antiseptic

INDICATIONS AND USAGE

Kills harmful bacteria that can be found on the skin.

WARNINGS

- Flammable. Keep away from fire or flame.
- For external use only
- If swallowed, get medical help or contact a Poison Control Center right away.
- Should solution enter eyes, flush immediately with water.

Ask a doctor before use if you have deep wounds, animal bites or serious burns.

Store out of reach of children.

DOSAGE AND ADMINISTRATION

Pump product in palm of hand and rub thoroughly until hands are dry. Do not rinse or wipe off foam.

INACTIVE INGREDIENT

Deionized water, Bis-PEG/PPG-20/20 Dimethicone, ethylcellulose, PEG-14M

PACKAGE LABEL

NPN #80005750

Stoko Refresh

Foaming Instant Hand Sanitizer

Mousse nettoyante instantanee pour les mains

Net Contents / Contenu Net: 800ml (27.04 fl.oz.)

Stock # / No. de Stock: 31869